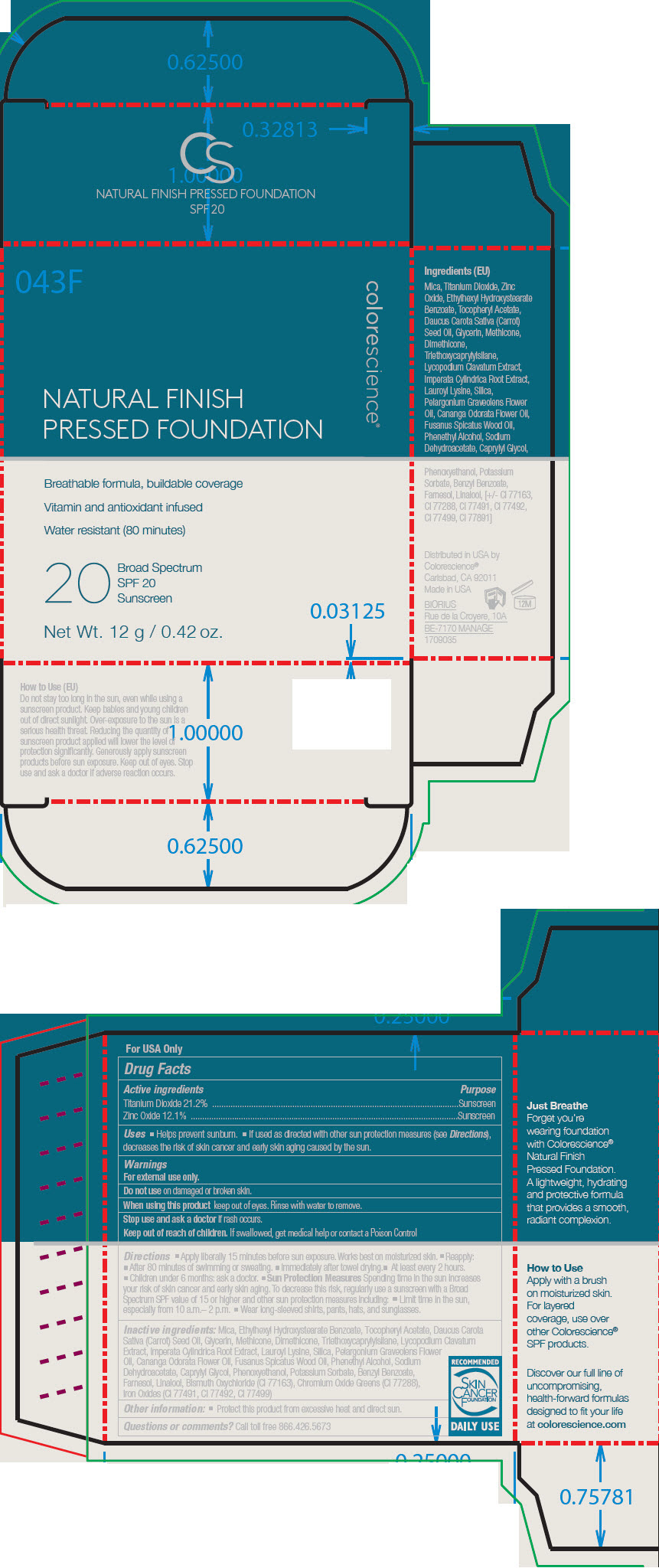 DRUG LABEL: Natural Finish Pressed Foundation SPF 20 Sunscreen
NDC: 68078-013 | Form: POWDER
Manufacturer: Colorescience
Category: otc | Type: HUMAN OTC DRUG LABEL
Date: 20241216

ACTIVE INGREDIENTS: Titanium Dioxide 212 mg/1 g; Zinc Oxide 120 mg/1 g
INACTIVE INGREDIENTS: Mica; BENZYL BENZOATE; .Alpha.-Tocopherol Acetate; Carrot Seed Oil; Glycerin; Methicone (20 Cst); Dimethicone; Triethoxycaprylylsilane; LYCOPODIUM CLAVATUM SPORE; Imperata Cylindrica Root; Lauroyl Lysine; Silicon Dioxide; Pelargonium Graveolens Flower Oil; YLANG-YLANG OIL; Santalum Spicatum Oil; Phenylethyl Alcohol; Sodium Dehydroacetate; Caprylyl Glycol; Phenoxyethanol; Potassium Sorbate; Bismuth Oxychloride; Chromic Oxide; FERRIC OXIDE RED; FERRIC OXIDE YELLOW; FERROSOFERRIC OXIDE

Natural Finish Pressed Foundation SPF 20 Sunscreen

Drug Facts

ACTIVE INGREDIENT

Active ingredients | Purpose
Titanium Dioxide 21.2% | Sunscreen
Zinc Oxide 12.1% | Sunscreen

Uses

- Helps prevent sunburn.
- If used as directed with other sun protection measures (see Directions), decreases the risk of skin cancer and early skin aging caused by the sun.

Warnings

For external use only.

Do not use on damaged or broken skin.

When using this product keep out of eyes. Rinse with water to remove.

Stop use and ask a doctor if rash occurs.

Keep out of reach of children. If swallowed, get medical help or contact a Poison Control

Directions

- Apply liberally 15 minutes before sun exposure. Works best on moisturized skin.
- Reapply:
  - After 80 minutes of swimming or sweating.
  - Immediately after towel drying.
  - At least every 2 hours.
- Children under 6 months: ask a doctor.
- Sun Protection Measures Spending time in the sun increases your risk of skin cancer and early skin aging. To decrease this risk, regularly use a sunscreen with a Broad Spectrum SPF value of 15 or higher and other sun protection measures including:
  - Limit time in the sun, especially from 10 a.m.– 2 p.m.
  - Wear long-sleeved shirts, pants, hats, and sunglasses.

Inactive ingredients

Mica, Ethylhexyl Hydroxystearate Benzoate, Tocopheryl Acetate, Daucus Carota Sativa (Carrot) Seed Oil, Glycerin, Methicone, Dimethicone, Triethoxycaprylylsilane, Lycopodium Clavatum Extract, Imperata Cylindrica Root Extract, Lauroyl Lysine, Silica, Pelargonium Graveolens Flower Oil, Cananga Odorata Flower Oil, Fusanus Spicatus Wood Oil, Phenethyl Alcohol, Sodium Dehydroacetate, Caprylyl Glycol, Phenoxyethanol, Potassium Sorbate, Benzyl Benzoate, Farnesol, Linalool, Bismuth Oxychloride (CI 77163), Chromium Oxide Greens (CI 77288), Iron Oxides (CI 77491, CI 77492, CI 77499)

Other information

- Protect this product from excessive heat and direct sun.

Questions or comments?

Call toll free 866.426.5673

Distributed in USA by
Colorescience®
Carlsbad, CA 92011

PRINCIPAL DISPLAY PANEL - 12 g Container Carton

colorescience®

NATURAL FINISH
PRESSED FOUNDATION

Breathable formula, buildable coverage

Vitamin and antioxidant infused

Water resistant (80 minutes)

20
Broad Spectrum
SPF 20
Sunscreen

Net Wt. 12 g / 0.42 oz.